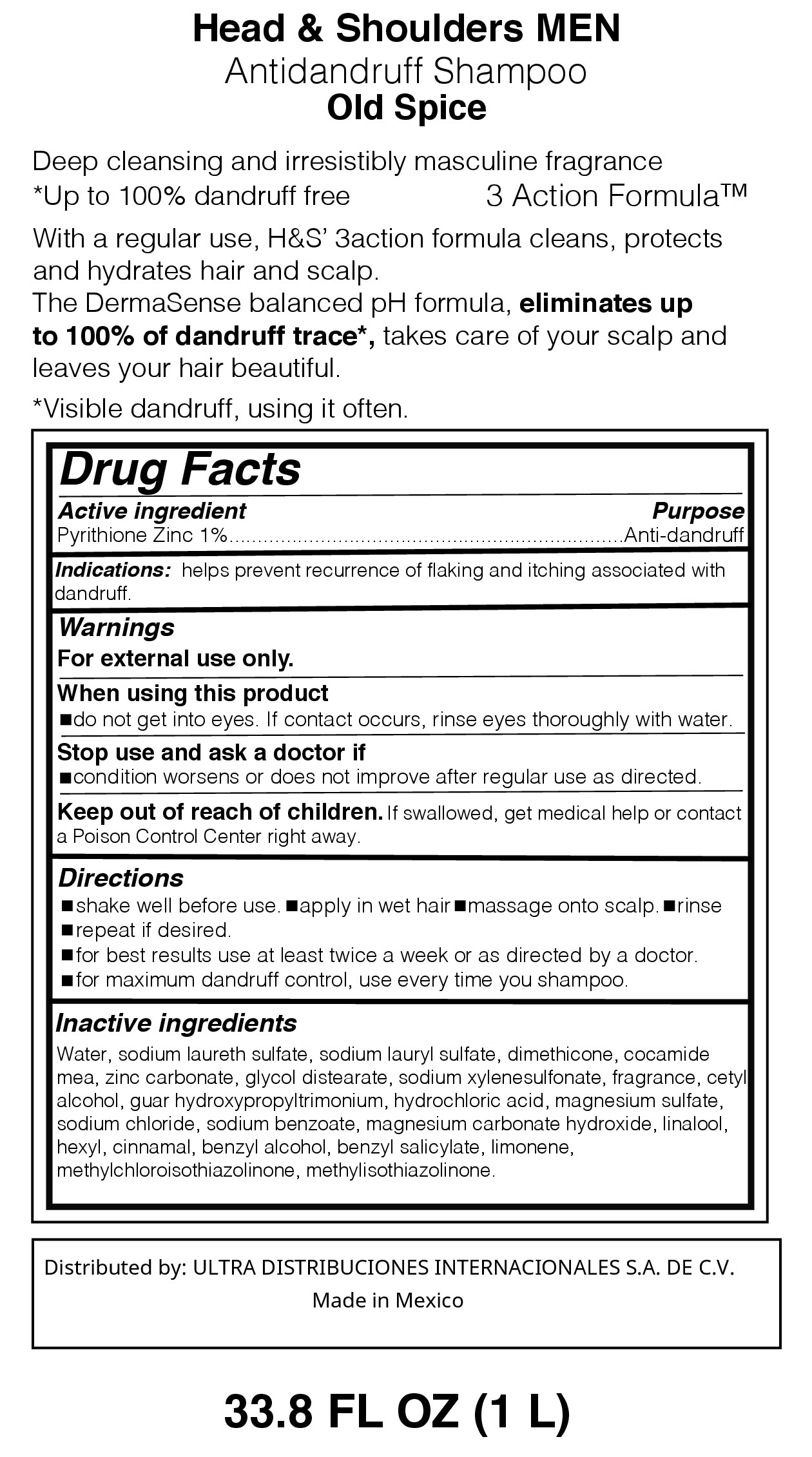 DRUG LABEL: HEAD AND SHOULDERS OLD SPICE
NDC: 72389-102 | Form: LOTION/SHAMPOO
Manufacturer: ULTRA DISTRIBUCIONES INTERNACIONALES, S.A. DE C.V.
Category: otc | Type: HUMAN OTC DRUG LABEL
Date: 20220114

ACTIVE INGREDIENTS: PYRITHIONE ZINC 1 g/100 mL
INACTIVE INGREDIENTS: LIMONENE, (+)-; WATER; SODIUM LAURYL SULFATE; SODIUM LAURETH SULFATE; GLYCOL DISTEARATE; LINALOOL, (-)-; MAGNESIUM CARBONATE HYDROXIDE; DIMETHICONE; .ALPHA.-HEXYLCINNAMALDEHYDE; SODIUM CHLORIDE; SODIUM XYLENESULFONATE; LAURIC MONOETHANOLAMIDE; METHYLISOTHIAZOLINONE; SODIUM BENZOATE; GUAR HYDROXYPROPYLTRIMONIUM CHLORIDE (1.7 SUBSTITUENTS PER SACCHARIDE); HYDROCHLORIC ACID; ZINC CARBONATE; METHYLCHLOROISOTHIAZOLINONE; CETYL ALCOHOL; BENZYL ALCOHOL; BENZYL SALICYLATE; MAGNESIUM SULFATE, UNSPECIFIED

Head and Shoulders Old Spice

Purpose

With Regular use, H&S 3action formula cleans, protects and hydrates hair and scalf.

The DermaSense balanced pH formula, eliminates up to 100% of dandruff trace*, takes care of your scalp and leaves your hair

beautiful,

*Visible dandruff, using it often.

Active Ingredient

Active Ingredient................................................................................Purpose

Pyrithione Zinc 1%.....................................................................Anti-dandruff

Warnings

for external use only.

When using this product

-do not get into eyes. If contact occurs, rinse thoroughly with water

Stop use and ask doctor if

condition worsens or does not improve after regular use as directed

Keep our of reach of children

If swallowed, get medical help or contact a Poison Control Center right away

Directions

-shake well before use - apply in wet hair - massage into scalp - rinse

-repeat as desired

-for best results use at least twice a week or as directed by a doctor

-for maximum dandruff control, use every time you shampoo

Inactive Ingredients

Water, sodium lauryl sulfate, sodium laureth sulfate, glycol distearate,

dimethicone, zinc carbonate, sodium chloride, sodium xylenesulfonate,

cocamidopropyl betaine, parfum, sodium benzoate, guar

hydroxypropyltrimonium chloride, hydrochloric acid, hexyl cinnamal,

linalool, magnesium carbonate hydroxide, methylchloroisothiazolinone,

FD&C Blue 1, methylisothiaolinone, D&C Red.33

Distributed by:

ULTRA DISTRIBUCIONES INTERNACIONALES, S.A. DE C.V.

Made in Mexico

Indications:

helps prevent recurrence of flaking and itching associated with dandruff